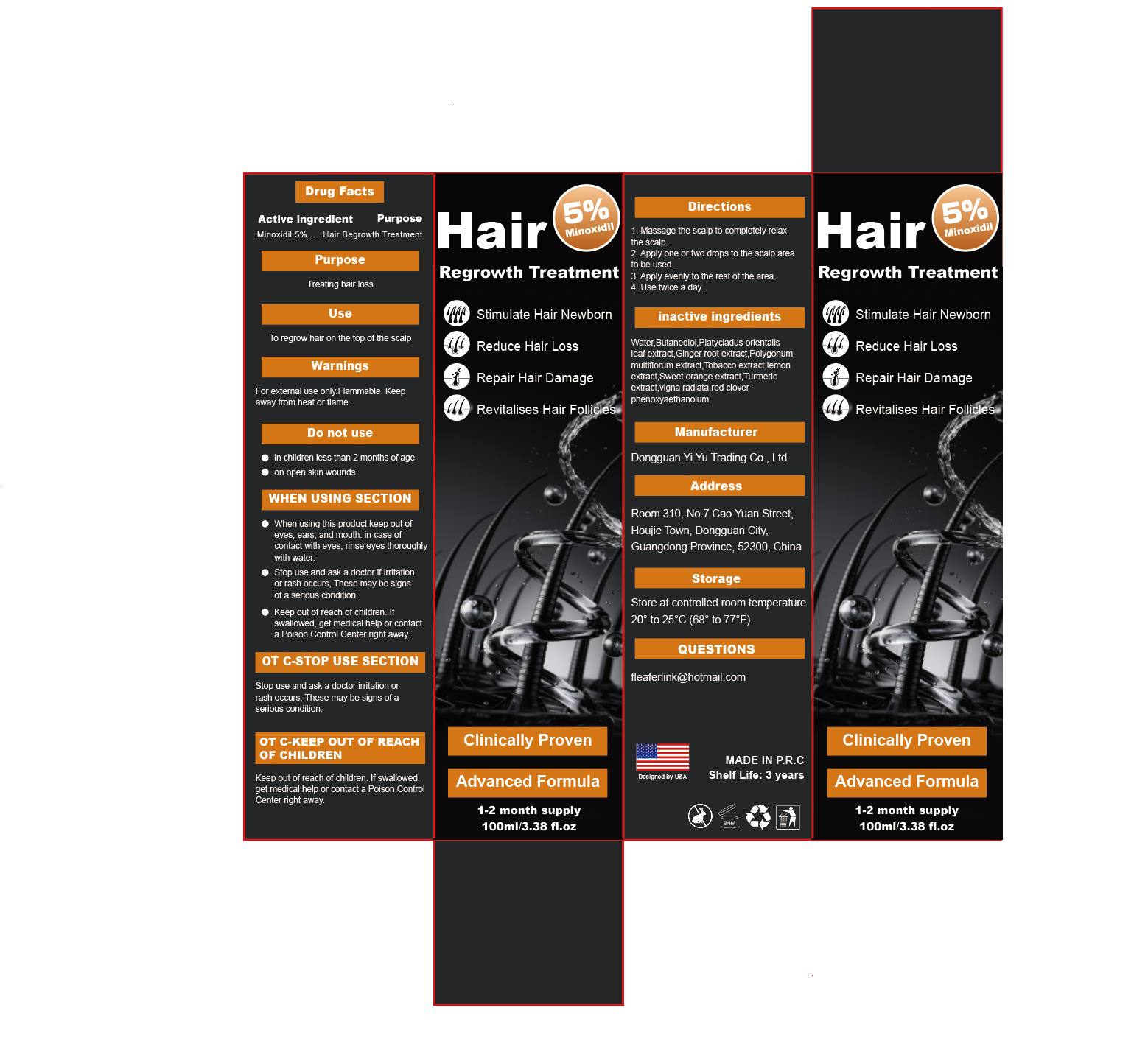 DRUG LABEL: Hair Regrowth Treatment
NDC: 85407-001 | Form: LIQUID
Manufacturer: Dongguan yiyu trading co., ltd
Category: otc | Type: HUMAN OTC DRUG LABEL
Date: 20250323

ACTIVE INGREDIENTS: MINOXIDIL 5 g/100 mL
INACTIVE INGREDIENTS: MUNG BEAN; WATER; BUTANEDIOL (MIXED ISOMERS); PLATYCLADUS ORIENTALIS LEAF; GINGER; RHEIN; TOBACCO LEAF; LEMON; ORANGE TERPENES; CURCUMIN; RED CLOVER; PHENOXYETHANOL

85407-001
Hair Regrowth Treatment

Active Ingredient(s)

minoxidil 5%

Purpose

Hair Begrowth Treatment

Use

To regrow hair on the top of the scalp

Warnings

For external use only.Flammable. Keep away from heat or flame.

Do not use

●in children less than 2 months of age
●on open skin wounds

●When using this product keep out of eyes, ears, and mouth. in case of contact with eyes, rinse eyes thoroughly with water
●Stop use and ask a doctor if iritation or rash occurs, These may be signs of a serious condition.
●Keep out of reach of children. If swallowed, get medical help or contact a Poison Control Center right away.

Stop use and ask a doctor iritation or rash occurs, These may be signs of a serious condition.

Keep out of reach of children. If swallowed, get medical help or contact a Poison Control Center right away.

Directions

1. Massage the scalp to completely relax the scalp.
2. Apply one or two drops to the scalp area to be used.
3. Apply evenly to the rest of the area.
4. Use twice a day.

Other information

Store at controlled room temperature 20° to25°C (68° to 77*F).

Inactive ingredients

Water, Butanediol,Platycladus orientalis leaf extract,Ginger root extract, Polygonum
multiflorum extract, Tobacco extract,lemon extract,Sweet orange extract, Turmeric
extract,vigna radiata,red clover phenoxyaethanolum